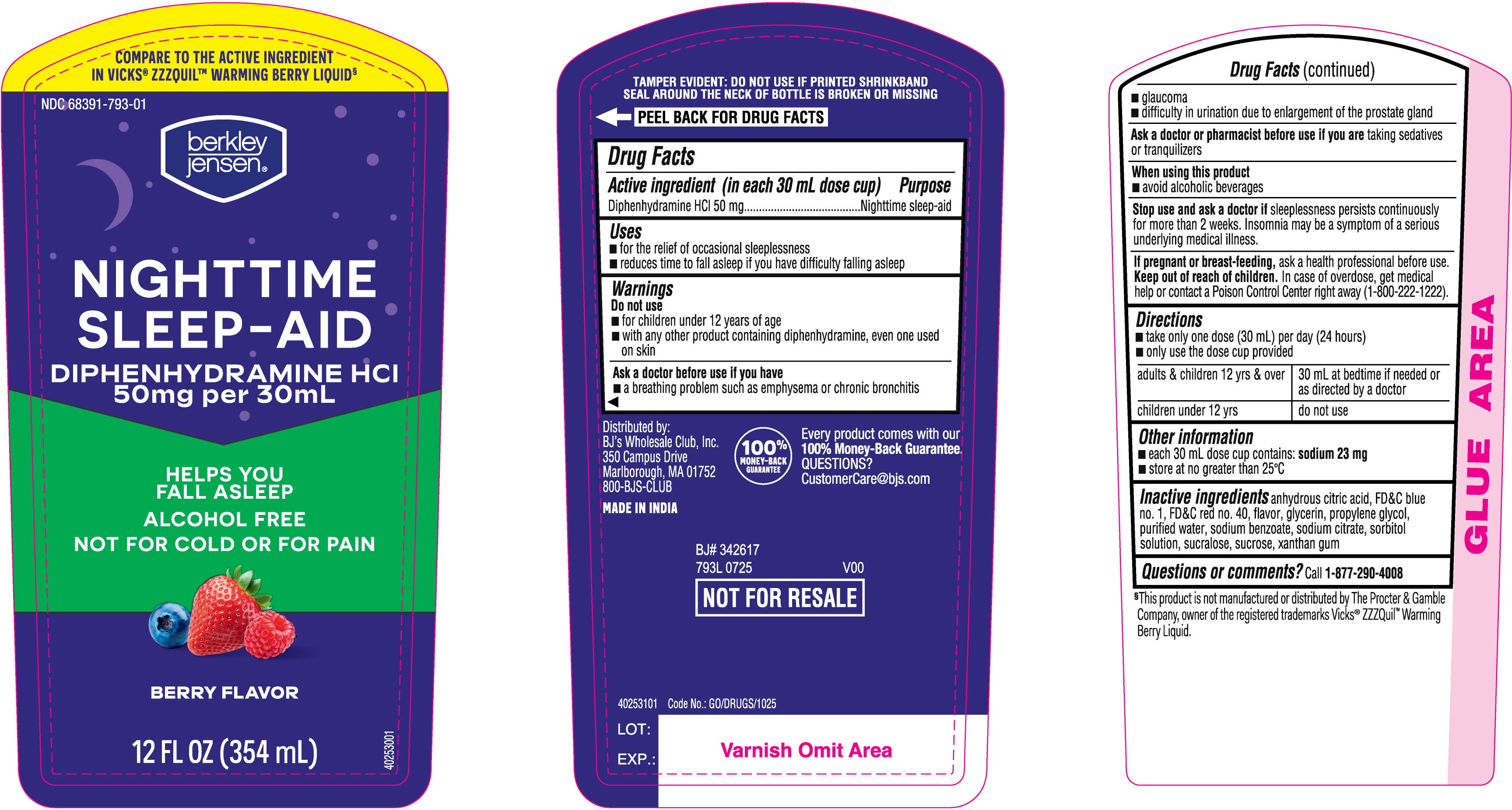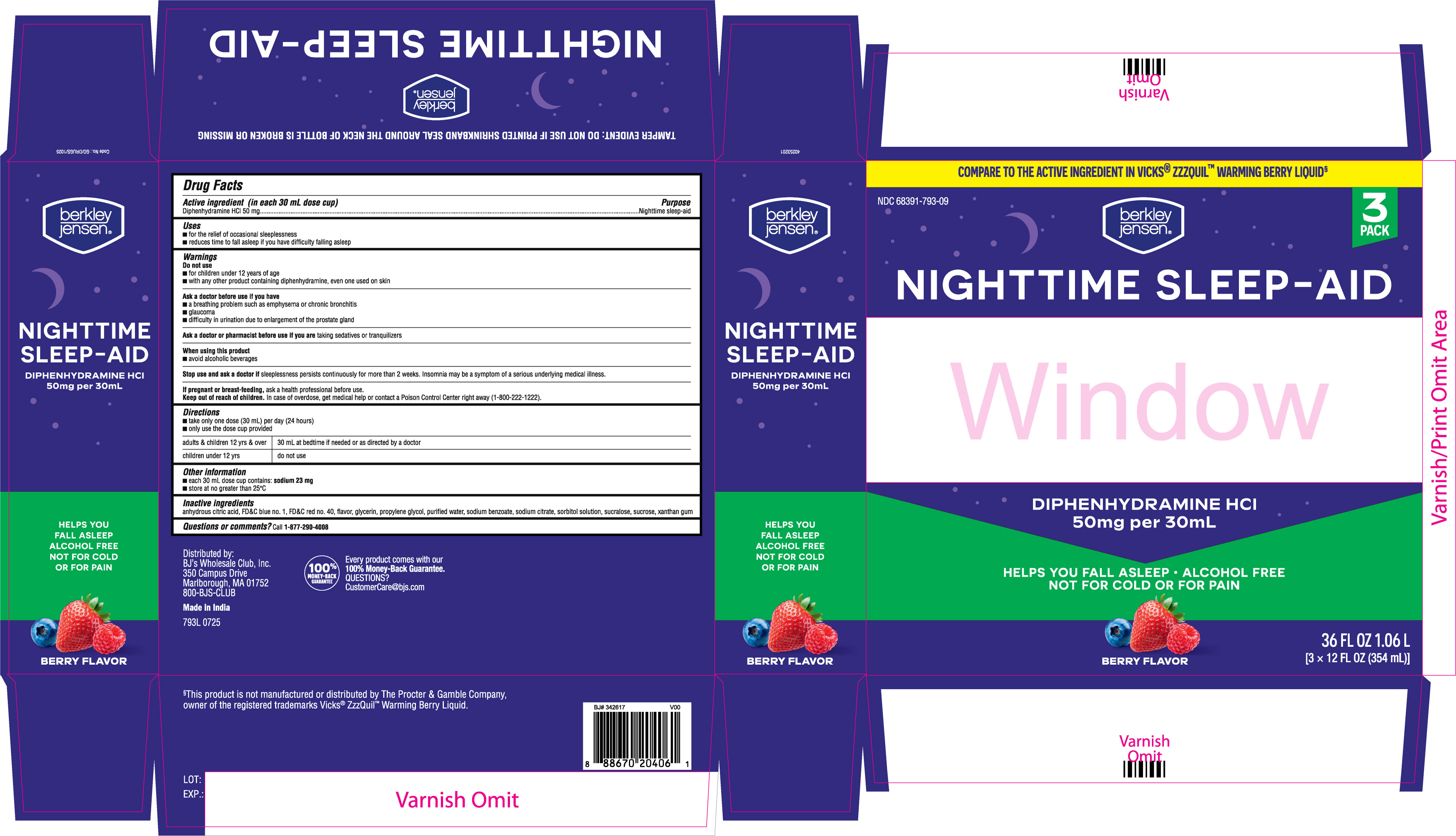 DRUG LABEL: Nighttime Sleep Aid
NDC: 68391-793 | Form: LIQUID
Manufacturer: BJWC (Berkley & Jensen / BJ's)
Category: otc | Type: HUMAN OTC DRUG LABEL
Date: 20250819

ACTIVE INGREDIENTS: DIPHENHYDRAMINE HYDROCHLORIDE 50 mg/30 mL
INACTIVE INGREDIENTS: FD&C RED NO. 40; PROPYLENE GLYCOL; SODIUM BENZOATE; SORBITOL SOLUTION; ANHYDROUS CITRIC ACID; XANTHAN GUM; SUCROSE; SUCRALOSE; FD&C BLUE NO. 1; GLYCERIN; WATER; SODIUM CITRATE, UNSPECIFIED FORM

BJs Diphenhydramine Hydrochloride 50 mg per 30 mL Liquid - Berry Flavor

Drug Facts

Active ingredient (in each 30 mL dose cup)

Diphenhydramine HCl 50 mg

Purpose

Nighttime sleep-aid

Uses

- for the relief of occasional sleeplessness
- reduces time to fall asleep if you have difficulty falling asleep

Warnings

Do not use

- for children under 12 years of age
- with any other product containing diphenhydramine, even one used on skin

Ask a doctor before use if you have

- a breathing problem such as emphysema or chronic bronchitis
- glaucoma
- difficulty in urination due to enlargement of the prostate gland

Ask a doctor or pharmacist before use if you are taking sedatives or tranquilizers

When using this product

- avoid alcoholic beverages

Stop use and ask a doctor if sleeplessness persists continuously for more than 2 weeks. Insomnia may be a symptom of a serious underlying medical illness.

PREGNANCY OR BREAST FEEDING

If pregnant or breast-feeding, ask a health professional before use.

Keep out of reach of children. In case of overdose, get medical help or contact a Poison Control Center right away (1-800-222-1222).

Directions

- take only one dose (30 mL) per day (24 hours)
- only use the dose cup provided

adults & children 12 yrs & over | 30 mL at bedtime if needed or as directed by a doctor
children under 12 yrs | do not use

Other information

- each 30 mL dose cup contains: sodium 23 mg
- store at no greater than 25°C

INACTIVE INGREDIENT

Inactive ingredients anhydrous citric acid, FD&C blue no. 1, FD&C red no. 40, flavor, glycerin, propylene glycol, purified water, sodium benzoate, sodium citrate, sorbitol solution, sucralose, sucrose, xanthan gum

Questions or comments? Call 1-877-290-4008

793L12 fl oz label

793L 36 fl oz carton